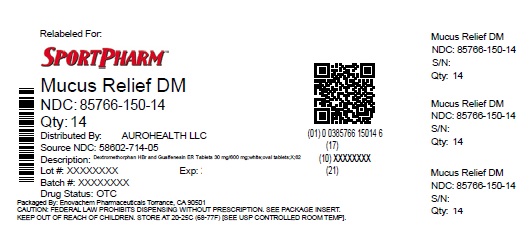 DRUG LABEL: Guaifenesin and Dextromethorphan HBr
NDC: 85766-150 | Form: TABLET, EXTENDED RELEASE
Manufacturer: Sportpharm LLC
Category: otc | Type: HUMAN OTC DRUG LABEL
Date: 20260218

ACTIVE INGREDIENTS: GUAIFENESIN 600 mg/1 1; DEXTROMETHORPHAN HYDROBROMIDE 30 mg/1 1
INACTIVE INGREDIENTS: SILICON DIOXIDE; HYPROMELLOSE, UNSPECIFIED; MAGNESIUM STEARATE; MICROCRYSTALLINE CELLULOSE; POVIDONE K90; POVIDONE K25; STARCH, CORN

Drug Facts

Active ingredients

(in each extended-release tablet)
Dextromethorphan Hydrobromide USP 30 mg
Guaifenesin USP 600 mg

Purposes

Cough suppressant
Expectorant

Uses

- helps loosen phlegm (mucus) and thin bronchial secretions to rid the bronchial passageways of bothersome mucus and make coughs more productive
  - temporarily relieves:
    - cough due to minor throat and bronchial irritation as may occur with the common cold or inhaled irritants
    - the intensity of coughing
    - the impulse to cough to help you get to sleep

Warnings

Do not use

- for children under 12 years of age
- if you are now taking a prescription monoamine oxidase inhibitor (MAOI) (certain drugs for depression, psychiatric or emotional conditions, or Parkinson’s disease), or for 2 weeks after stopping the MAOI drug. If you do not know if your prescription drug contains an MAOI, ask a doctor or pharmacist before taking this product.

Ask a doctor before use if you have

- persistent or chronic cough such as occurs with smoking, asthma, chronic bronchitis, or emphysema
- cough accompanied by too much phlegm (mucus)

When using this product

- do not use more than directed

Stop use and ask a doctor if

- cough lasts more than 7 days, comes back, or occurs with fever, rash, or persistent headache. These could be signs of a serious illness

If pregnant or breast-feeding,

ask a health professional before use.

Keep out of reach of children.

In case of overdose, get medical help or contact a Poison Control Center (1-800-222-1222) right away.

Directions

- do not crush, chew, or break extended-release tablet
- take with a full glass of water
- this product can be administered without regard for timing of meals
- adults and children 12 years and older: 1 or 2 extended-release tablets every 12 hours; not more than 4 extended-release tablets in 24 hours
- children under 12 years of age: do not use

Other information

- store at 20° to 25°C (68° to 77°F)

Inactive ingredients

colloidal silicon dioxide, hypromellose, magnesium stearate, microcrystalline cellulose, povidone, pregelatinized starch (maize)

Questions?

call 1-855-274-4122